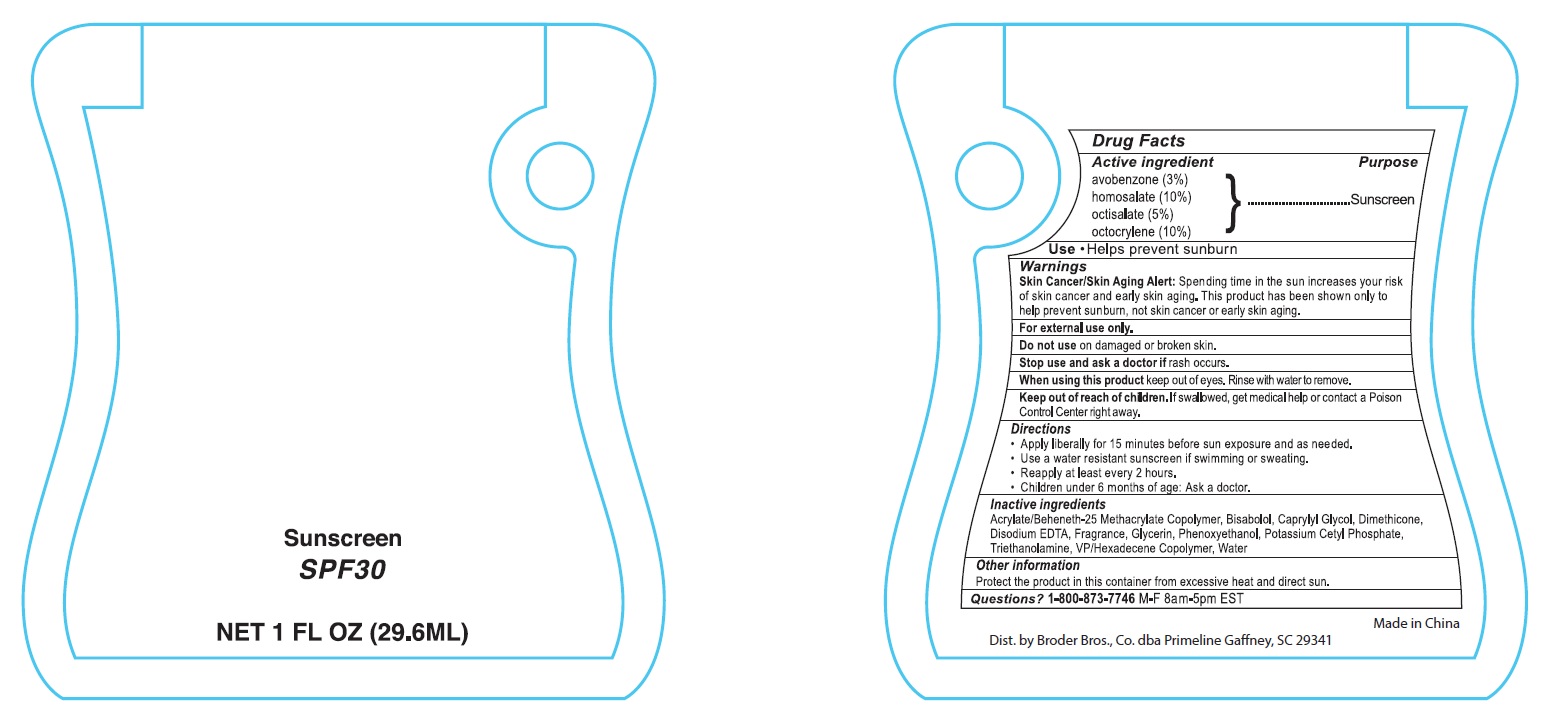 DRUG LABEL: Sunscreen SPF30
NDC: 71513-708 | Form: LOTION
Manufacturer: Broder Bros Prime Line
Category: otc | Type: HUMAN OTC DRUG LABEL
Date: 20251117

ACTIVE INGREDIENTS: AVOBENZONE 30 mg/1 mL; HOMOSALATE 100 mg/1 mL; OCTISALATE 50 mg/1 mL; OCTOCRYLENE 100 mg/1 mL
INACTIVE INGREDIENTS: LEVOMENOL; GLYCERIN; WATER; VINYLPYRROLIDONE/HEXADECENE COPOLYMER; TROLAMINE; POTASSIUM CETYL PHOSPHATE; CAPRYLYL GLYCOL; DIMETHICONE; EDETATE DISODIUM ANHYDROUS; PHENOXYETHANOL

PL-1849

Active ingredients

avobenzone (3%)

homosalate (10%)

octisalate (5%)

octocrylene (10%)

Purpose

Sunscreen

INDICATIONS AND USAGE

Use • Helps prevent sunburn

Warnings

Skin Cancer/Skin Aging Alert: Spending time in the sun increases your risk of skin cancer and early skin aging. This product has been shown only to help prevent sunburn, not skin cancer or early skin aging.

For external use only.

Do not use on damaged or broken skin.

Stop use and ask a doctor if rash occurs.

When using this product keep out of eyes. Rinse with water to remove.

Keep out of reach of children. If swallowed, get medical help or contact a Poison Control Center right away.

Directions

- Apply liberally for 15 minutes before sun exposure and as needed.
- Use a water resistant sunscreen if swimming or sweating.
- Reapply at least every 2 hours.
- Children under 6 months of age: Ask a doctor.

Inactive ingredients

Acrylate/Beheneth-25 Methacrylate Copolymer, Bisabolol, Caprylyl Glycol, Dimethicone, Disodium EDTA, Fragrance, Glycerin, Phenoxyethanol, Potassium Cetyl Phosphate, Triethanolamine, VP/Hexadecene Copolymer, Water

Other information

Protect the product in this container from excessive heat and direct sun.

QUESTIONS

Questions?1-800-873-7746 M-F 8am-5pm EST

PACKAGE LABEL

Sunscreen

SPF30

Net 1 FL OZ (29.6ML)

Dist. by Broder Bros., Co. dba Primeline Gaffney, SC 29341

Made in China